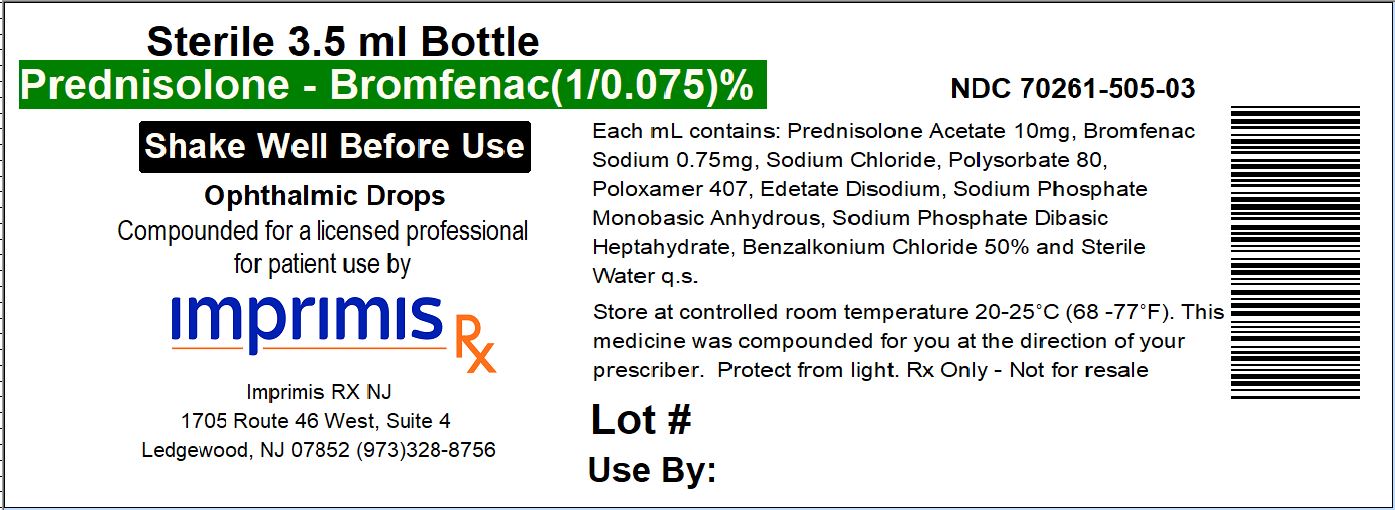 DRUG LABEL: Pred-Brom
NDC: 70261-505 | Form: SUSPENSION/ DROPS
Manufacturer: ImprimisRx NJ
Category: prescription | Type: HUMAN PRESCRIPTION DRUG LABEL
Date: 20180301

ACTIVE INGREDIENTS: BROMFENAC 0.75 mg/1 mL; PREDNISOLONE ACETATE 10 mg/1 mL

STORAGE AND HANDLING

Store at 20° to 25° C (68° to 77° F)